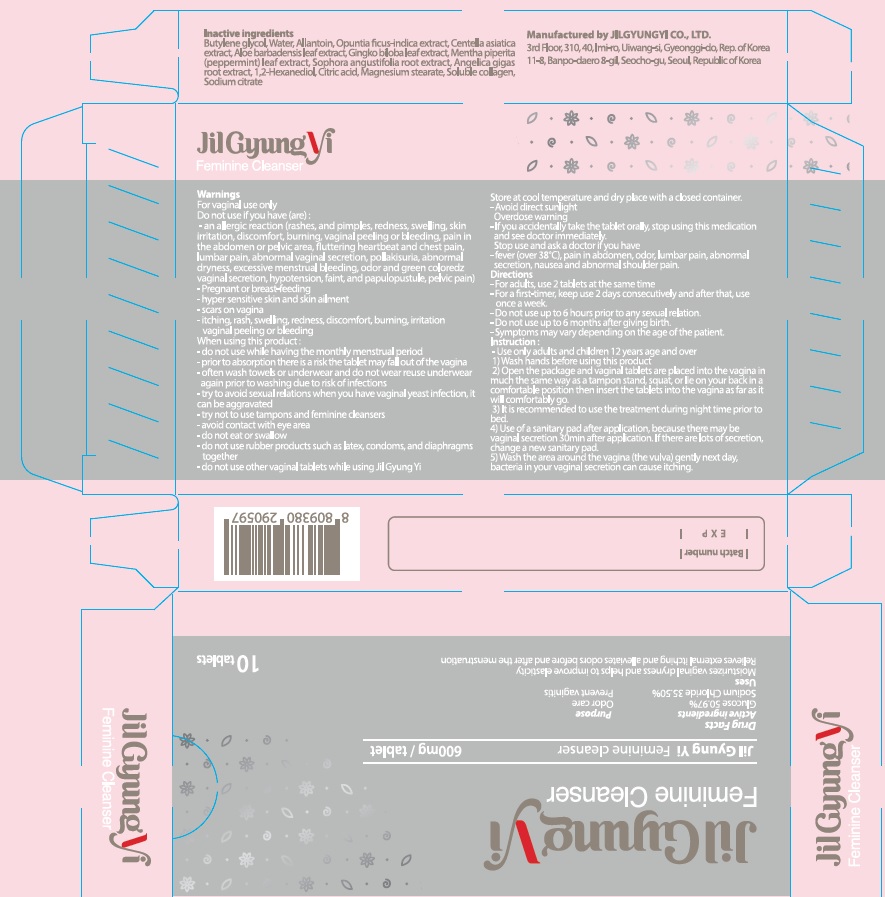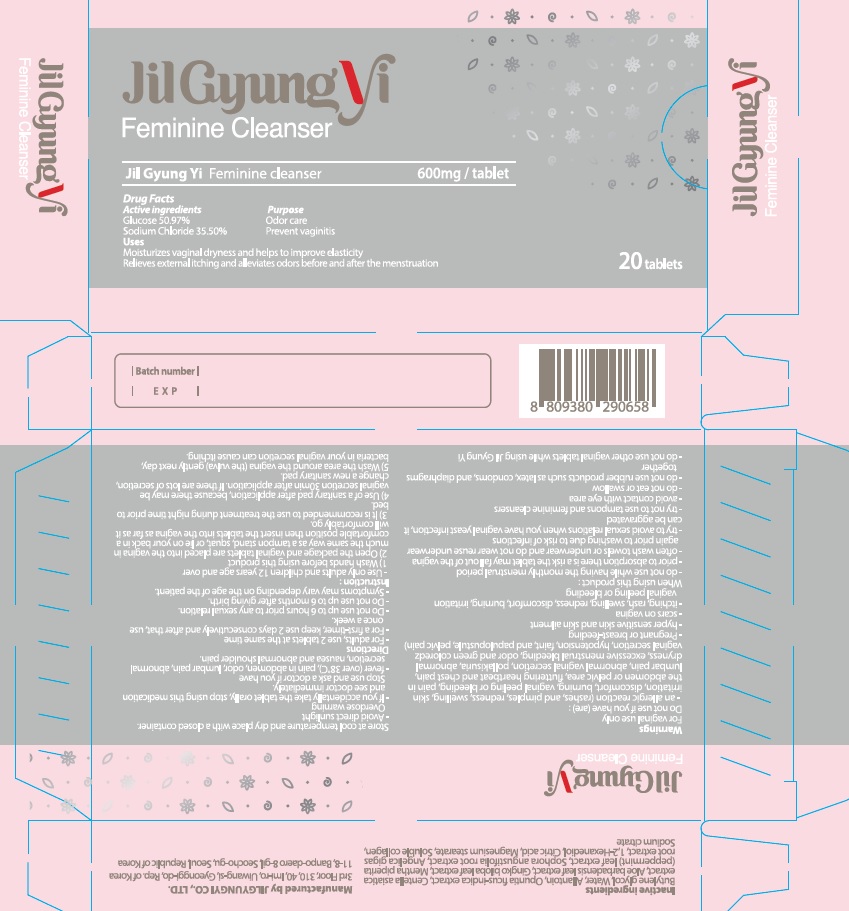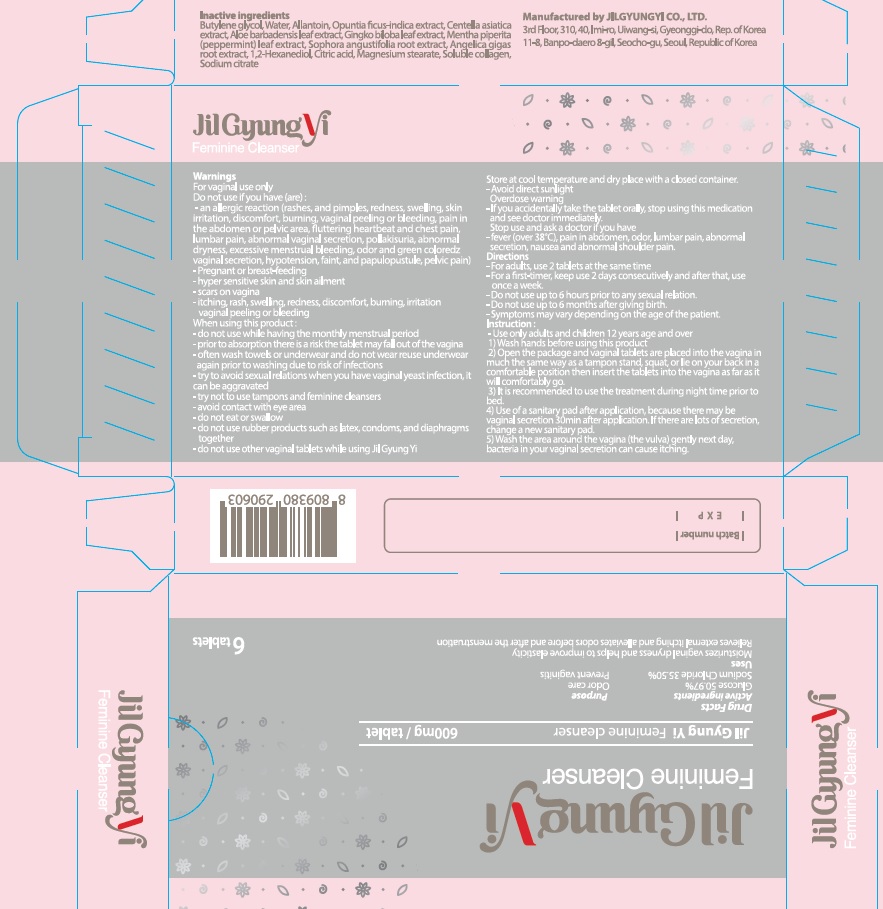 DRUG LABEL: JILGYUNGYI
NDC: 73004-010 | Form: TABLET
Manufacturer: JILGYUNGYI CO.,LTD.
Category: otc | Type: HUMAN OTC DRUG LABEL
Date: 20211112

ACTIVE INGREDIENTS: ANHYDROUS DEXTROSE 305.82 mg/600 mg; Sodium Chloride 213 mg/600 mg
INACTIVE INGREDIENTS: Butylene glycol; Water; Allantoin

ACTIVE INGREDIENT

Active Ingredient: Glucose 50.97%, Sodium Chloride 35.50%

INACTIVE INGREDIENT

Inactive Ingredients:

Butylene glycol, Water, Allantoin, Opuntia ficus-indica extract, Centella asiatica extract, Aloe barbadensis leaf extract, Gingko biloba leaf extract, Mentha piperita(peppermint) leaf extract, Sophora angustifolia root extract, Angelica gigas root extract, 1,2-Hexanediol, Citric acid, Magnesium stearate, Soluble collagen, Sodium citrate

PURPOSE

Purpose: Odor care, Prevent vaginitis

WARNINGS

For vaginal use only
Do not use if you have (are)
- an allergic reaction (rashes, and pimples, redness, swelling, skin irritation, discomfort, burning, vaginal peeling or bleeding, pain in the abdomen or pelvic area, fluttering heartbeat and chest pain, lumbar pain, abnormal vaginal secretion, pollakisuria, abnormal dryness, excessive menstrual bleeding, odor and green colored vaginal secretion, hypotension, faint, and papulopustule, pelvic pain)
- pregnant
- hyper sensitive skin and skin ailment
- scars on vagina
- itching, rash, swelling, redness, discomfort, burning, irritation vaginal peeling or bleeding
When using this product
- do not use while having the monthly menstrual period
- prior to absorption there is a risk the tablet may fall out of the vagina
- often wash towels or underwear and do not wear reuse underwear again prior to washing due to risk of infections
- try to avoid sexual relations when you have vaginal yeast infection, it can be aggravated
- try not to use tampons and feminine cleansers
- avoid contact with eye area
- do not eat or swallow
- do not use rubber products such as latex, condoms, and diaphragms together
- do not use other vaginal tablets while using Jil Gyung Yi
If pregnant or breast-feeding, do not use.

Store at cool temperature and dry place with a closed container. Avoid direct sunlight

Overdose warning
- If you accidentally take the tablet orally, stop using this medication and see doctor immediately.

Stop use and ask a doctor if you have
- fever (over 38°C), pain in abdomen, odor, lumbar pain, abnormal secretion, nausea and abnormal shoulder pain.

KEEP OUT OF REACH OF CHILDREN

INDICATIONS & USAGE

Uses:

Moisturizes vaginal dryness and helps to improve elasticity
Relieves external itching and alleviates odors before and after the menstruation

DOSAGE & ADMINISTRATION

Directions:

For adults – 2 tablets at the same time
- For a first-timer, keep use 2 days consecutively and after that, use once a week.
- Do not use up to 6 hours prior to any sexual relation.
- Do not use up to 6 months after giving birth.
- Symptoms may vary depending on the age of the patient.

Directions
- Use only adults and children 12 years age and over
1) Wash hands before using this product
2) Open the package and vaginal tablets are placed into the vagina in much the same way as a tampon stand, squat, or lie on your back in a comfortable position then insert the tablets into the vagina as far as it will comfortably go.
3) It is recommended to use the treatment during night time prior to bed.
4) Use of a sanitary pad after application, because there may be vaginal secretion 30min after application. If there are lots of secretion, change a new sanitary pad.
5) Wash the area around the vagina (the vulva) gently next day, bacteria in your vaginal secretion can cause itching.